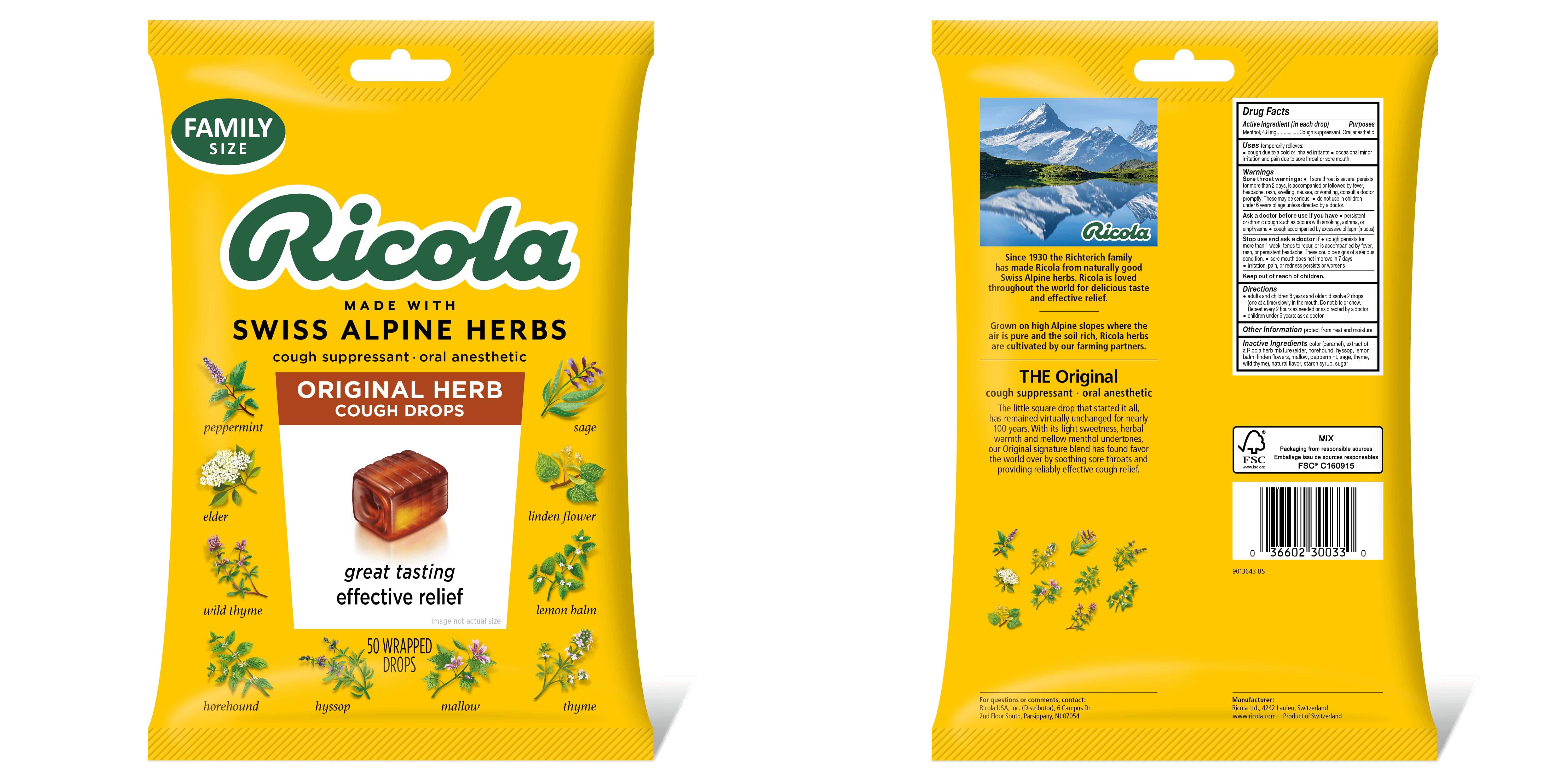 DRUG LABEL: THE ORIGINAL NATURAL HERB COUGH DROPS
NDC: 63667-955 | Form: LOZENGE
Manufacturer: Ricola USA Inc.
Category: otc | Type: HUMAN OTC DRUG LABEL
Date: 20250422

ACTIVE INGREDIENTS: MENTHOL 4.8 mg/1 1
INACTIVE INGREDIENTS: SUCROSE; CARAMEL

THE ORIGINAL NATURAL HERB COUGH DROPS COUGH SUPPRESSANT THROAT DROPS

Drug Facts

Purpose

Cough suppressant, Oral anesthetic

Active Ingredient (in each drop)

Menthol, 4.8 mg

Uses

temporarily relieves:

- cough due to a cold or inhaled irritants
- occasional minor irritation and pain due to sore throat or sore mouth

Warnings

Sore throat warnings:

- if sore throat is severe, persists for more than 2 days, is accompanied or followed by fever, headache, rash, swelling, nausea, or vomiting, consult a doctor promptly. These may be serious.
- do not use in children under 6 years of age unless directed by a doctor.

Ask doctor before use if you have

- persistent chronic cough such as occurs with smoking, asthma, or emphysema
- cough accompanied by excessive phlegm (mucus)

Stop use and ask a doctor if

- cough persists for more than 1 week, tends to recur, or is accompanied by fever, rash, or persistent headache. These could be signs of a serious condition.
- sore mouth does not improve in 7 days
- irritation, pain, or redness persists or worsens

Directions

- adults and children 6 years and older: dissolve 2 drops (one at a time) slowly in the mouth. Repeat every 2 hours as needed or as directed by a doctor
- children under 6 years: ask a doctor

Other Information

Store in a dry place

Inactive Ingredients

color (caramel), extract of a Ricola herb mixture (elder, horehound, hyssop, lemon balm, linden flowers, mallow, peppermint, sage, thyme, wild thyme), natural flavor, starch syrup, sugar